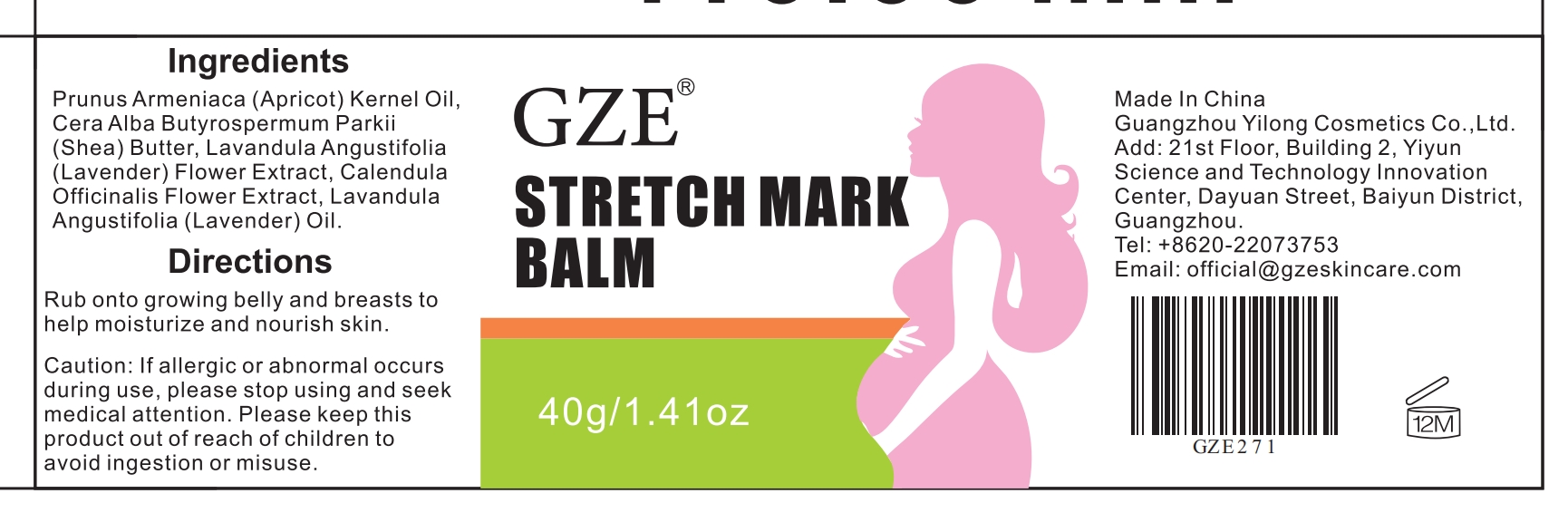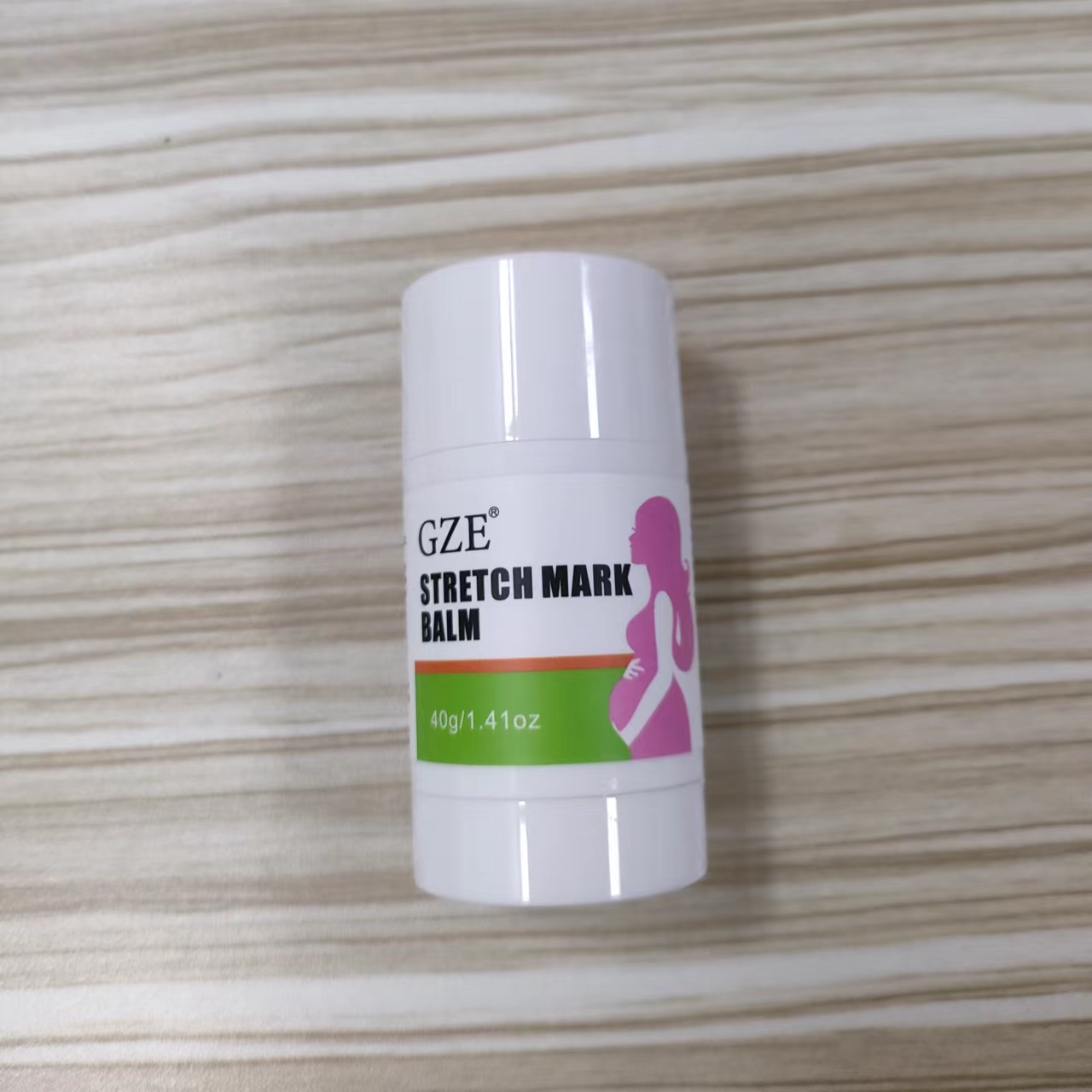 DRUG LABEL: GZE STRETCH MARK BALM
NDC: 83566-271 | Form: STICK
Manufacturer: Guangzhou Yilong Cosmetics Co., Ltd
Category: otc | Type: HUMAN OTC DRUG LABEL
Date: 20240703

ACTIVE INGREDIENTS: APRICOT KERNEL OIL 47.42 g/100 g
INACTIVE INGREDIENTS: BUTYROSPERMUM PARKII (SHEA) BUTTER UNSAPONIFIABLES; LAVENDER OIL; LAVANDULA ANGUSTIFOLIA FLOWER; CALENDULA OFFICINALIS FLOWER; PEG-8 BEESWAX

GZE STRETCH MARK BALM

ACTIVE INGREDIENT

Apricot Kernel Oil

INACTIVE INGREDIENT

Cera Alba

Butyrospermum Parkii (Shea) Butter

Lavandula Angustifolia (Lavender) Flower Extract

Calendula Officinalis Flower Extract

Lavandula Angustifolia (Lavender) Oil

PURPOSE

Moisturize and nourish skin.

INDICATIONS AND USAGE

Rub onto growing belly and breasts to help moisturize and nourish skin.

WARNINGS

For external use only.

Stop use and ask a doctor if rash occurs.

Do not use on damaged or broken skin.

When using this product keep out of eyes. Rinse with water to remove.

Keep out of reach of children. If swallowed, get medical help or contact a Poison Control Center right away.

DOSAGE AND ADMINISTRATION

After showering and drying the body Apply in a circular motion on the desired spot on the body.